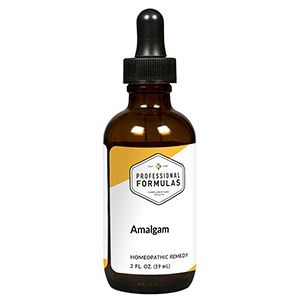 DRUG LABEL: Amalgam
NDC: 63083-6003 | Form: LIQUID
Manufacturer: Professional Complementary Health Formulas
Category: homeopathic | Type: HUMAN OTC DRUG LABEL
Date: 20190815

ACTIVE INGREDIENTS: TILLETIA CARIES 30 [hp_X]/59 mL; BOS TAURUS GINGIVA 30 [hp_X]/59 mL; BOS TAURUS BONE 30 [hp_X]/59 mL; TREPONEMA DENTICOLA 30 [hp_X]/59 mL; ISATIS TINCTORIA ROOT 30 [hp_X]/59 mL; SILVER 30 [hp_X]/59 mL; GOLD 30 [hp_X]/59 mL; SILICON DIOXIDE 30 [hp_X]/59 mL; EPICHLOROHYDRIN 30 [hp_X]/59 mL; FLUORINE 30 [hp_X]/59 mL; MERCURIUS SOLUBILIS 30 [hp_X]/59 mL; XANTHAN GUM 30 [hp_X]/59 mL; NICKEL 30 [hp_X]/59 mL; PALLADIUM 30 [hp_X]/59 mL; PLATINUM 30 [hp_X]/59 mL; ZINC CATION 30 [hp_X]/59 mL; SODIUM FLUORIDE 30 [hp_X]/59 mL; TITANIUM 30 [hp_X]/59 mL
INACTIVE INGREDIENTS: ALCOHOL; WATER

X3

ACTIVE INGREDIENTS

Caries 30X, 60X
Gingivitis 30X, 60X
Osteomyelitis 30X, 60X
Periodontitis 30X, 60X
Root ostitis 30X, 60X
and all the following at 30X, 60X, 100X:
Amalgam
Dental gold
Dental plastics
Epoxies
Fluorine
Mercurius solubilis
Misc. binders
Nickel
Palladium
Platinum
Setting agents
Silver (6 types)
Sodium fluoride
Titanium

QUESTIONS

Professional Formulas

PO Box 2034 Lake Oswego, OR 97035

INDICATIONS

For the temporary relief of swollen, red, or tender gums, occasional bad breath, minor toothache, occasional headache, irritability, or fatigue due to sensitivity to or exposure to oral/dental materials.*

PURPOSE

*Claims based on traditional homeopathic practice, not accepted medical evidence. Not FDA evaluated.

WARNINGS

Consult a doctor if condition worsens or symptoms persist. Not intended for use by individuals with retained amalgams. Keep out of the reach of children. In case of overdose, get medical help or contact a poison control center right away. If pregnant or breastfeeding, ask a healthcare professional before use.

Keep out of the reach of children.

PREGNANCY OR BREAST FEEDING

If pregnant or breastfeeding, ask a healthcare professional before use.

DIRECTIONS

Place drops under tongue 30 minutes before/after meals. Adults and children 12 years and over: Take 10 drops up to 3 times per day. Consult a physician for use in children under 12 years of age.

OTHER INFORMATION

Tamper resistant. If seal is broken, do not use. After opening, close container tightly and store at room temperature away from heat.

INACTIVE INGREDIENTS

20% ethanol, purified water.

LABEL

Est 1985

Professional Formulas

Complementary Health

Amalgam

Homeopathic Remedy

2 FL. OZ. (59 mL)